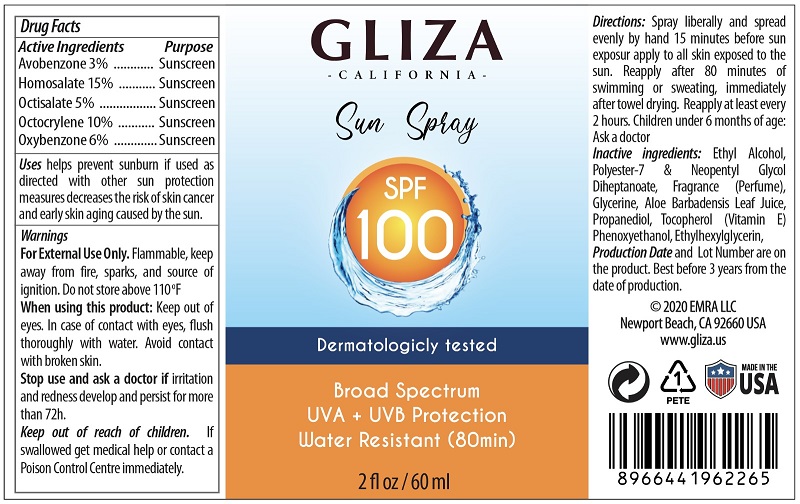 DRUG LABEL: GLIZA BODY MIST SUNSCREEN BROAD SPECTRUM SPF 100
NDC: 77903-002 | Form: SPRAY
Manufacturer: EMRA LLC
Category: otc | Type: HUMAN OTC DRUG LABEL
Date: 20200519

ACTIVE INGREDIENTS: AVOBENZONE 1.8 mg/60 mL; HOMOSALATE 9 mg/60 mL; OCTISALATE 3 mg/60 mL; OCTOCRYLENE 6 mg/60 mL; OXYBENZONE 3.6 mg/60 mL
INACTIVE INGREDIENTS: ALCOHOL; POLYESTER (ADIPIC ACID, 1,6-HEXANEDIOL, NEOPENTYL GLYCOL); FRAGRANCE LAVENDER & CHIA F-153480; GLYCERIN; ALOE VERA LEAF; PROPANEDIOL; TOCOPHEROL; PHENOXYETHANOL; 2-ETHYLHEXYL GLYCIDYL ETHER

GLIZA BODY MIST SUNSCREEN BROAD SPECTRUM SPF 100

Active Ingredient(s)

Avobenzone 3%
Homosalate 15%
Octisalate 5%
Octocrylene 10%
Oxybenzone 6%

Purpose

Sunscreen

Use

Uses helps prevent sunburn if used as directed with other sun protection measures decreases the risk of skin cancer
and early skin aging caused by the sun.

Warnings

For External Use Only. Flammable, keep away from fire, sparks, and source of
ignition. Do not store above 110 oF

When using this product:

Keep out of eyes. In case of contact with eyes, ush thoroughly with water. Avoid contact
with broken skin.

Stop use and ask a doctor if irritation and redness develop and persist for more
than 72h.

Keep out of reach of children. If swallowed get medical help or contact a
Poison Control Centre immediately.

Directions :

Spray liberally and spread evenly by hand 15 minutes before sun
exposur apply to all skin exposed to the sun. Reapply after 80 minutes of
swimming or sweating, immediately after towel drying. Reapply at least every
2 hours. Children under 6 months of age:
Ask a doctor

Stop use and ask a doctor if irritation or rash occurs. These may be signs of a serious condition.

Inactive ingredients

Ethyl Alcohol, Polyester-7 & Neopentyl Glycol Diheptanoate, Fragrance (Perfume),
Glycerine, Aloe Barbadensis Leaf Juice, Propanediol, Tocopherol (Vitamin E)
Phenoxyethanol, Ethylhexylglycerin,

Package Label - Principal Display Panel

0.06 L (60 mL) NDC: 77903-002-01